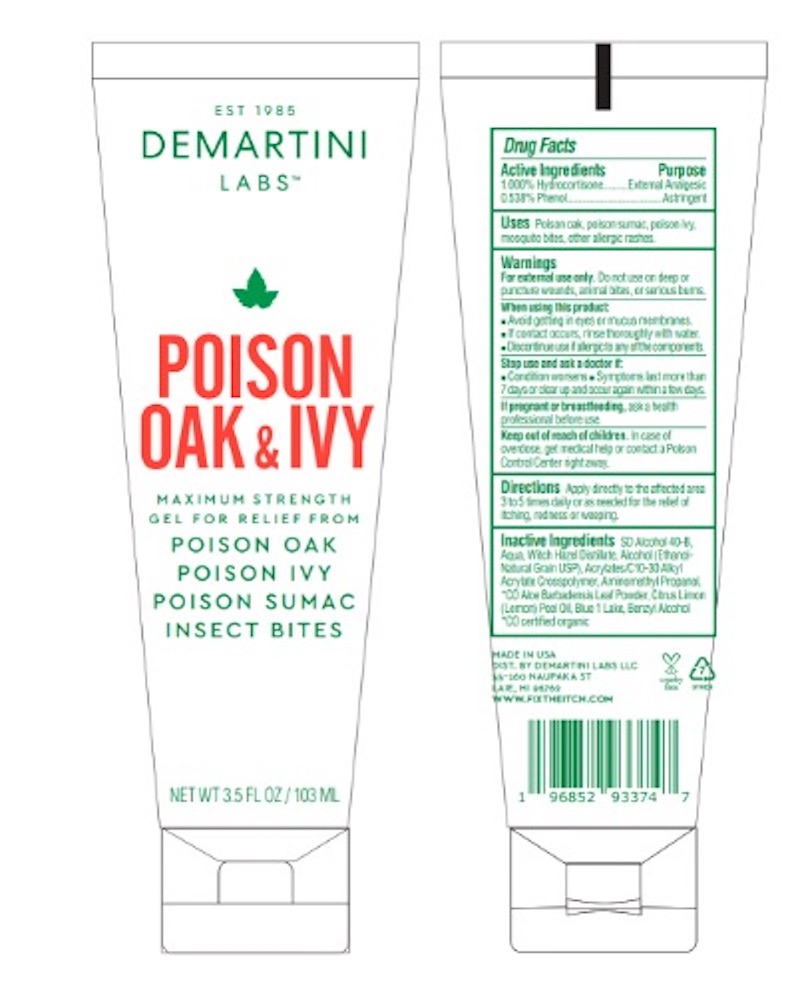 DRUG LABEL: POISON OAK AND IVY
NDC: 57479-102 | Form: GEL
Manufacturer: DeMartini Spring Hill Pharmacy, Inc.
Category: otc | Type: HUMAN OTC DRUG LABEL
Date: 20230824

ACTIVE INGREDIENTS: HYDROCORTISONE 1.3 g/103 mL; PHENOL 0.54 g/103 mL
INACTIVE INGREDIENTS: ALCOHOL; CARBOMER COPOLYMER TYPE A (ALLYL PENTAERYTHRITOL CROSSLINKED); ALOE VERA LEAF; BENZYL ALCOHOL; FD&C BLUE NO. 1; LEMON JUICE; WITCH HAZEL; AMINOMETHYL PROPANEDIOL; WATER

ACTIVE INGREDIENT

HYDROCORTISONE (1%)

PHENOL (0.538%)

PURPOSE

EXTERNAL ANALGESIC

ASTRINGENT

INDICATIONS AND USAGE

USES: POISON OAK, POISON SUMAC, POISON IVY, MOSQUITO BITES, OTHER ALLERGIC RASHES.

WARNINGS

WARNINGS: FOR EXTERNAL USE ONLY. DO NOT USE ON EEP OR PUNCTURE WOUNDS, ANIMAL BITES, OR SERIOUS BURNS.

KEEP OUT OF REACH OF CHILDREN. IN CASE OF OVERDOSE, GET MEDICAL HELP ORCONTACT A POISON CONTROL CENTER RIGHT AWAY.

DOSAGE AND ADMINISTRATION

DIRECTIONS FOR USE: APPLY DIRECTLY TO THE RASH AREA 3 TO 5 TIMES DAILY OR AS NEEDED FOR THE RELIEF OF ITCHING, REDNESS OR WEEPING.

INACTIVE INGREDIENT

INACTIVE INGREDIENTS: SD Alcohol 40-B, Aqua, Witch Hazel Distillate, Alcohol (Ethanol-Natural Grain USP), Acrylates/C10-30, Alkyl Acrylate Crosspolymer, Aminomethyl Propanol, *CO Aloe Vera Leaf Powder, Citrus Limon (Lemon) Peel Oil, Benzyl Alcohol, Blue 1 *CO certified organic

When using this product
• Avoid getting in eyes or mucus membranes. If contact occurs rinse thoroughly with water.
• Discontinue use if allergic to any of the components.

Stop use and ask a doctor if
• condition worsens
• symptoms last more than 7 days or clear up and occur again within a few days.

PREGNANCY OR BREAST FEEDING

If pregnant or breast feeding, ask a health professional before use.